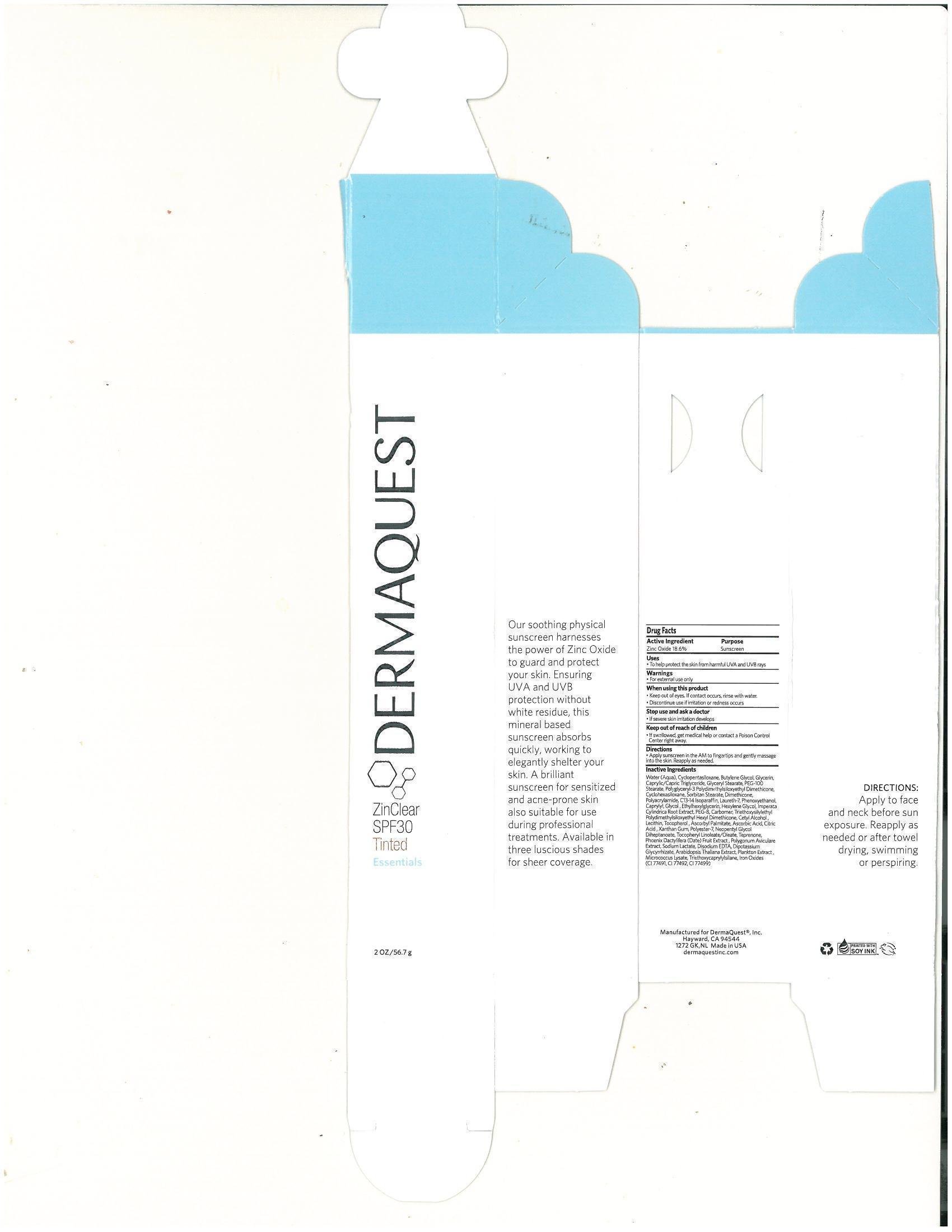 DRUG LABEL: ZinClear SPF 30 Tinted
NDC: 62742-4064 | Form: CREAM
Manufacturer: Allure Labs Inc.
Category: otc | Type: HUMAN OTC DRUG LABEL
Date: 20140421

ACTIVE INGREDIENTS: ZINC OXIDE 186 mg/1 g
INACTIVE INGREDIENTS: WATER; CYCLOMETHICONE 5; BUTYLENE GLYCOL; GLYCERIN; MEDIUM-CHAIN TRIGLYCERIDES; GLYCERYL MONOSTEARATE  ; PEG-100 STEARATE; CYCLOMETHICONE 6 ; SORBITAN MONOSTEARATE; DIMETHICONE; POLYACRYLAMIDE (10000 MW); C13-14 ISOPARAFFIN; LAURETH-7; PHENOXYETHANOL ; CAPRYLYL GLYCOL; ETHYLHEXYLGLYCERIN; HEXYLENE GLYCOL; IMPERATA CYLINDRICA ROOT; POLYETHYLENE GLYCOL 400 ; CETYL ALCOHOL; TOCOPHEROL; ASCORBYL PALMITATE; ASCORBIC ACID; CITRIC ACID MONOHYDRATE; XANTHAN GUM; POLYESTER-7; NEOPENTYL GLYCOL DIHEPTANOATE; TEPRENONE; DATE ; POLYGONUM AVICULARE TOP; SODIUM LACTATE; EDETATE DISODIUM; GLYCYRRHIZINATE DIPOTASSIUM; ARABIDOPSIS THALIANA; TRIETHOXYCAPRYLYLSILANE; FERRIC OXIDE RED ; FERRIC OXIDE YELLOW; FERROSOFERRIC OXIDE

Drug Facts

Active Ingredient:

Zinc Oxide - 18.6%

Purpose:Sunscreen

Uses:

To help protect the skin from harmful UVA and UVB Rays

Warnings:

For External Use only

When using this product

- Keep out of eyes. If contact occurs, rinse with water
- Discontinue use if irritation or redness occurs

Stop use and ask a doctor

- if severe skin irritation develops

Keep out of reach of children

- if swallowed, get medical help or contact a Poison Control Center right away

Directions

- Apply sunscreen in the AM to fingertips and gently massage into the skin. Reapply as needed

Inactive Ingredients:

Water (Aqua), Cyclopentasiloxane, Butylene Glycol, Glycerin, Caprylic/Capric Triglyceride, Glyceryl Stearate, PEG-100 Stearate, Polyglyceryl-3 Polydimethylsiloxytethyl Dimethicone, Cyclohexasiloxane, Sorbitan Stearate, Dimethicone, Polyacrylamide, C13-14 Isoparaffin, Laureth-7, Phenoxyethanol, Caprylyl, Glycol, Ethylhexylglycerin, Hexylene Glycol, Imperata Cylindrica Root Extract, PEG-8, Carbomer, Triethoxysilylethyl Polydimethylsiloxyethyl Hexyl Dimethicone, Cetyl Alcohol, Lecithin, Tocopherol, Ascorbyl Palmitate, Ascorbic Acid, Citric Acid, Xanthan Gum, Polyester-7, Neopentyl Glycol Diheptanoate, Tocopheryl Linoleate/Oleate, Teprenone, Phoenix Dactylifera (Date) Fruit Extract, Polygonum Aviculare Extract, Sodium Lactate, Disodium EDTA, Dipotassium Glycrrihizate, Arabidopsis THaliana Extract, Plankton Extract, Micrococcus Lysate, Triethoxycaprylysilane, Iron Oxides (CI77491, CI77492, CI77499)